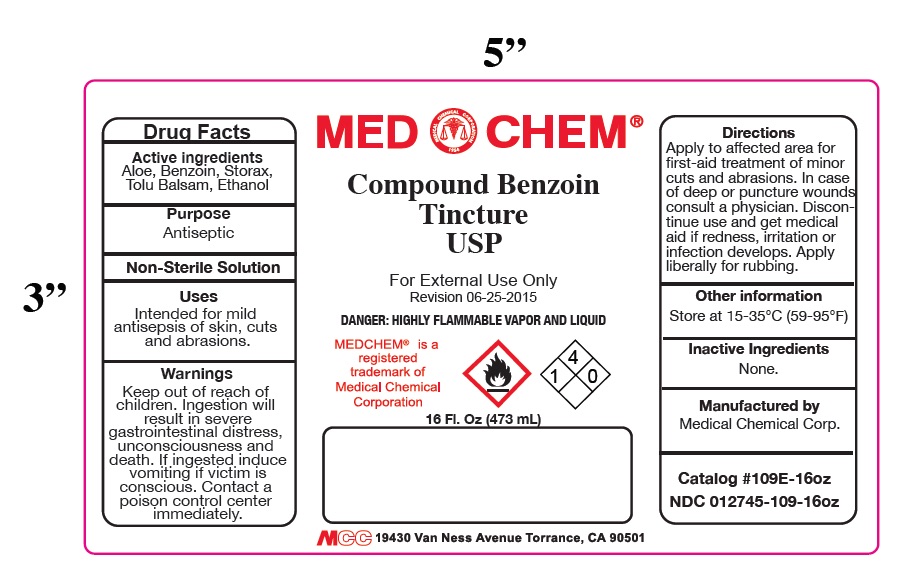 DRUG LABEL: Compound Benzoin Tincture
NDC: 12745-109 | Form: LIQUID
Manufacturer: Medical Chemical Corporation
Category: otc | Type: HUMAN OTC DRUG LABEL
Date: 20250731

ACTIVE INGREDIENTS: BENZOIN RESIN 10 g/100 mL
INACTIVE INGREDIENTS: WATER

Compound Benzoin Tincture Label

Active Ingredients: Aloe, Benzoin, Storax, Tolu Balsam, Ethanol

Purpose: Antiseptic

KEEP OUT OF REACH OF CHILDREN

Warnings: Keep out of reach of children. Ingestion will result in severe gastrointestinal distress, unconsciousness and death. If ingested induce vomiting if the victim is conscious. Contact a poison control center immediately.

INDICATIONS AND USAGE

Directions: Apply to affected area for first-aid treatment of minor cuts and abrasions. Discontinue use and get medical aid if redness, irritation or infection develops. In case of deep or puncture wounds consult a physician.

WARNINGS

Warnings: Keep out of reach of children. Ingestion will result in a severe gastrointestinal distress, unconsciousness and death. If ingested induce vomiting if victim is conscious. Contact a poison control center immediately.

DOSAGE AND ADMINISTRATION

Directions: Apply to affected area for first-aid treatment of minor cuts and abrasions. Discontinue use and get medical aid if redness, irritation or infection develops. In case of deep or puncture wounds consult a physician.

INACTIVE INGREDIENT

Enter section text here

PACKAGE LABEL

benzoinlabel.jpg